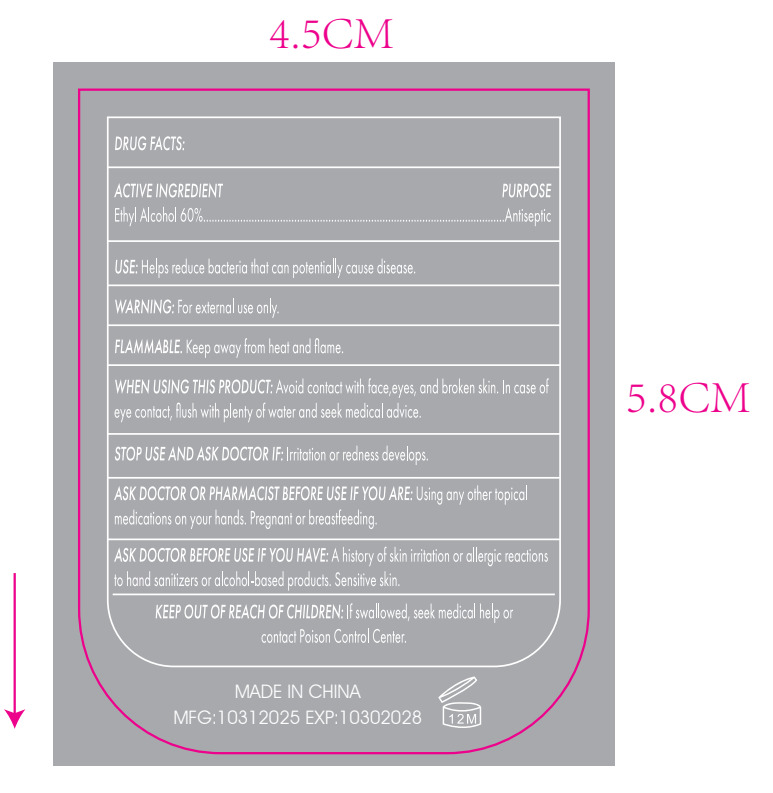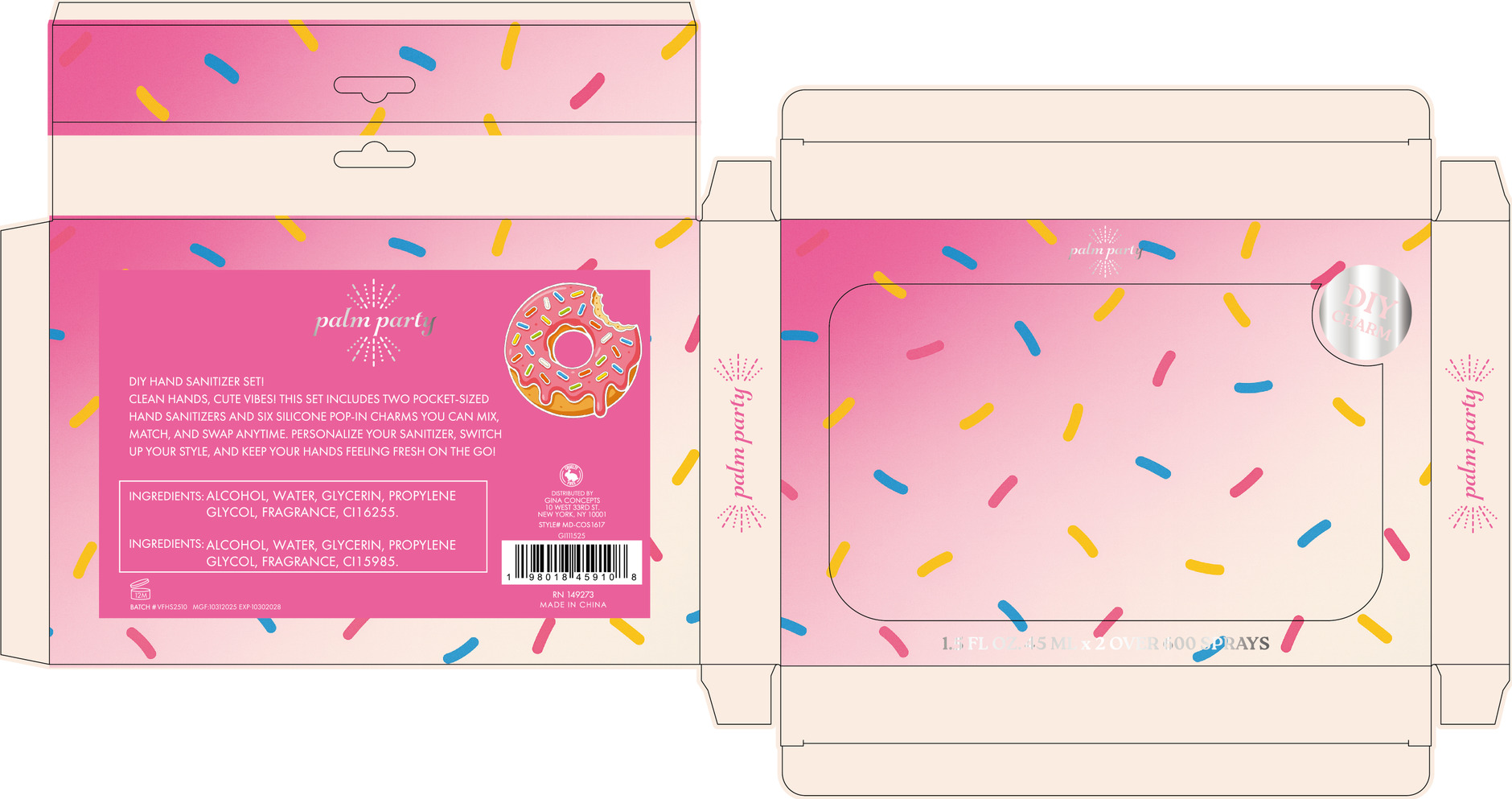 DRUG LABEL: hand sanitizer
NDC: 87426-001 | Form: LIQUID
Manufacturer: JINHUA YINKOU COSMETICS CO.,LTD
Category: otc | Type: HUMAN OTC DRUG LABEL
Date: 20260202

ACTIVE INGREDIENTS: ALCOHOL 60 mL/100 mL
INACTIVE INGREDIENTS: WATER; GLYCERIN; PROPYLENE GLYCOL; CI 16255

87426-001

Active Ingredient(s)

Ethyl Alcohol 60%

Purpose

Antiseptic

Use

Helps reduce bacteria that can potentially cause disease.

Warnings

For external use only.

Do not use on open skin wounds.

WHEN USING THIS PRODUCT: Avoid contact with face,eyes, and broken skin. In case of
eye contact, flush with plenty of water and seek medical advice.

STOP USE AND ASK DOCTOR IF: Irritation or redness develops.

KEEP OUT OF REACH OF CHILDREN: If swallowed, seek medical help or
contact Poison Control Center.

Directions

1. Take liquid: press the pump head of the hand sanitizer bottle and squeeze out a proper amount of hand sanitizer according to the size of the hand.

2. Rubbing: Apply hand sanitizer evenly to all parts of hands, including palms, backs of hands, fingers, finger joints, fingernails and wrists.

3. Rinse: Rinse your hands with flowing water, and rinse the hand sanitizer thoroughly.

4. Dry: Dry your hands with a clean towel or disposable paper towel.

Other information

FLAMMABLE. Keep away from heat and flame.

Inactive ingredients

WATER, GLYCERIN , PROPYLENE GLYCOL , FRAGRANCE , CI 16255